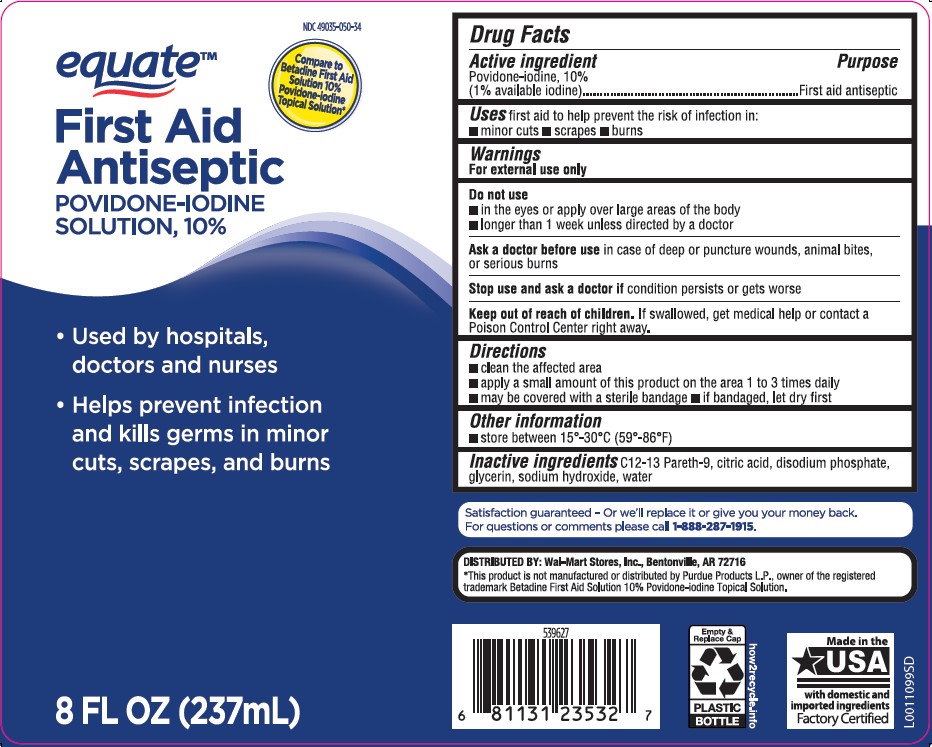 DRUG LABEL: First Aid Antiseptic
NDC: 49035-050 | Form: SOLUTION
Manufacturer: Walmart Inc.
Category: otc | Type: HUMAN OTC DRUG LABEL
Date: 20260227

ACTIVE INGREDIENTS: POVIDONE-IODINE 10 mg/1 mL
INACTIVE INGREDIENTS: GLYCERIN; SODIUM HYDROXIDE; WATER; C12-13 PARETH-9; CITRIC ACID MONOHYDRATE; SODIUM PHOSPHATE, DIBASIC, ANHYDROUS

Equate 050.002/050AE
Povidone-Iodine Solution, 10%

Active ingredient

Povidone-iodine, 10% (1% available iodine)

Purpose

First aid antiseptic

Use

first aid to help prevent the risk of infection in:

- minor cuts
- scrapes
- burns

Warnings

For external use only

Do not use

- in the eyes or apply over large areas of the body
- longer than 1 week unless directed by a doctor

Ask a doctor before use

in case of deep or puncture wounds, animal bites, or serious burns

Stop use and ask a doctor if

- condition persists or gets worse

Keep out of reach of children.

If swallowed, get medical help or contact a Poison Control Center right away.

Directions

- clean the affected area
- apply a small amount of this product on the area 1 to 3 times daily
- may be covered with a sterile bandage
- If bandaged, let dry first

Other information

- store between 15º-30ºC (59º-86ºF)

Inactive ingredients

C12-13 Pareth-9, citric acid, disodium phosphate, glycerin, sodium hydroxide, water

ADVERSE REACTION

Satisfaction guaranteed - Or we'll replace it or give you your money back.

For questions or comments please call 1-888-287-1915.

DISTRIBUTED BY: Wal-Mart Stores, Inc., Bentonville, AR 72716

Disclaimer

*This product is not manufactured or distributed by Purdue Products, LP, owner of the registered trademark Betadine First Aid Solution 10% Povidone-iodine Topical Solution.

principal display panel

NDC 49035-050-34

equate™

Compare to Betadine First Aid Solution 10% Povidone-iodine Topical Solution*

First Aid Antiseptic

Povidone-Iodine Solution, 10%

- Used by hospitals, doctors and nurses
- Helps prevent infection and kills germs in minor cuts, scrapes, and burns

8 FL OZ (237 mL)